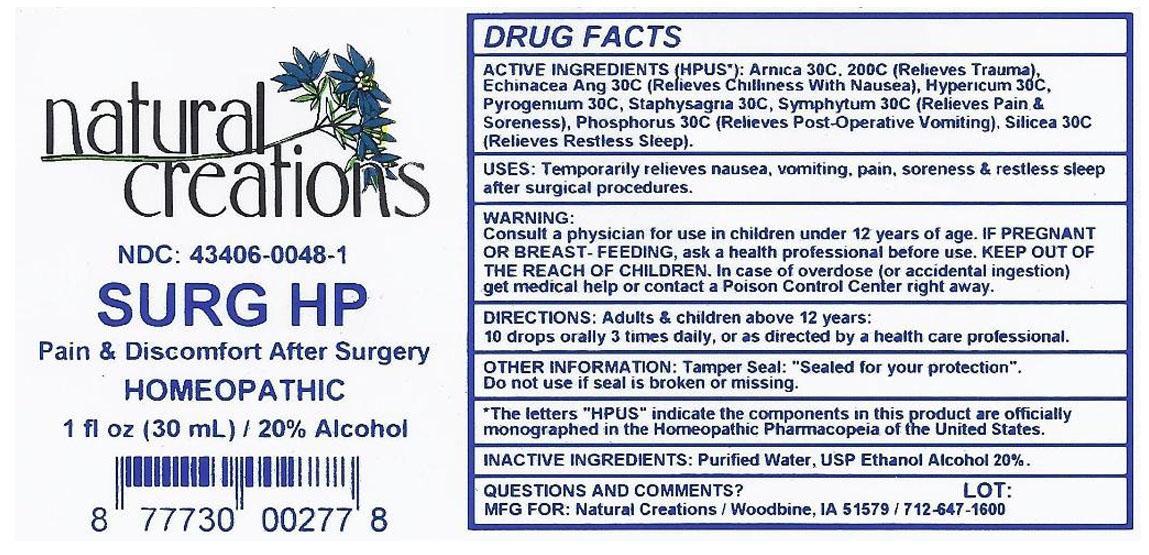 DRUG LABEL: SURG HP
NDC: 43406-0048 | Form: LIQUID
Manufacturer: Natural Creations, Inc.
Category: homeopathic | Type: HUMAN PRESCRIPTION DRUG LABEL
Date: 20121121

ACTIVE INGREDIENTS: ECHINACEA ANGUSTIFOLIA 30 [hp_C]/1 mL; HYPERICUM PERFORATUM 30 [hp_C]/1 mL; PHOSPHORUS 30 [hp_C]/1 mL; RANCID BEEF 30 [hp_C]/1 mL; SILICON DIOXIDE 30 [hp_C]/1 mL; DELPHINIUM STAPHISAGRIA SEED 30 [hp_C]/1 mL; COMFREY ROOT 30 [hp_C]/1 mL; ARNICA MONTANA ROOT 30 [hp_C]/1 mL; ARNICA MONTANA ROOT 200 [hp_C]/1 mL
INACTIVE INGREDIENTS: WATER; ALCOHOL

SURG HP

ACTIVE INGREDIENT

ACTIVE INGREDIENTS (HPUS*): Echinacea Angustifolia 30C, Hypericum Perforatum 30C, Phosphorus 30C, Pyrogenium 30C, Silicea 30C, Staphysagria 30C, Symphytum Officinale 30C, Arnica Montana 30C, Arnica Montana 200C

INDICATIONS AND USAGE

USES: Temporarily relieves nausea, vomiting, pain, soreness & restless sleep after surgical procedures.

WARNING:

Consult a physician for use in children under 12 years of age. IF PREGNANT OR BREAST-FEEDING, ask a health care professional before use. KEEP OUT OF THE REACH OF CHILDREN. In case of overdose (or accidental ingestion) get medical help or contact a Poison Control Center right away.

DOSAGE AND ADMINISTRATION

DIRECTIONS: Adults and children above 12 years: 10 drops orally 3 times daily, or as directed by a health care professional.

OTHER INFORMATION: Tamper Seal: "Sealed for your protection."

Do not use if seal is broken or missing.

REFERENCES

*The letters "HPUS" indicate the components in the product are officially monographed in the Homeopathic Pharmacopeia of United States.

INACTIVE INGREDIENTS: Purified Water, USP Ethanol Alcohol 20%

QUESTIONS AND COMMENTS?

MFG FOR: Natural Creations / Woodbine, IA / 51579 712.647.1600

LOT:

PURPOSE

USES: Temporarily relieves nausea, vomiting, pain, soreness, & restless sleep after surgical procedures.

KEEP OUT OF REACH OF CHILDREN

KEEP OUT OF THE REACH OF CHILDREN. In case of overdose (or accidental ingestion) get medical help or contact a Poison Control Center.

PACKAGE LABEL

NDC: 43406-0048-1

SURG HP

Pain & Discomfort After Surgery

HOMEOPATHIC

1 fl oz (30 mL) / 20% Alcohol

UPC: 877730002778